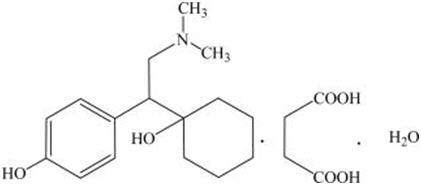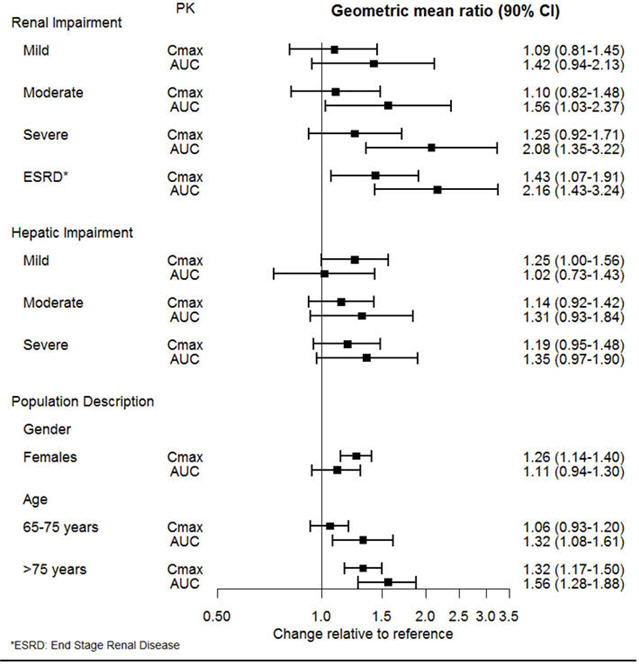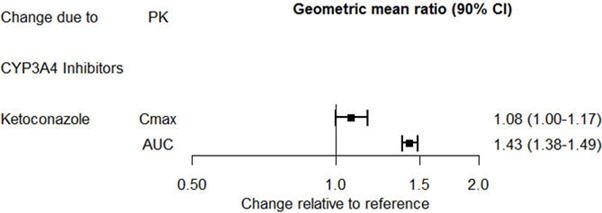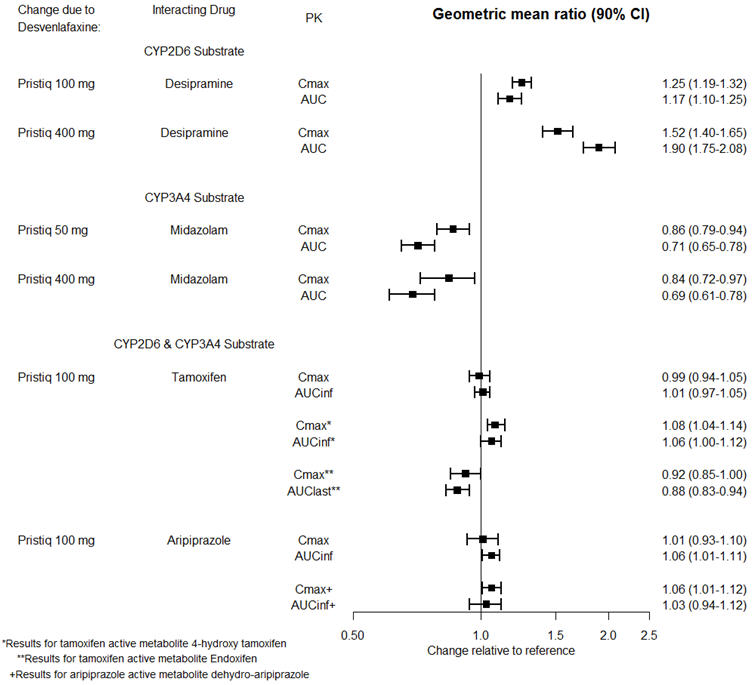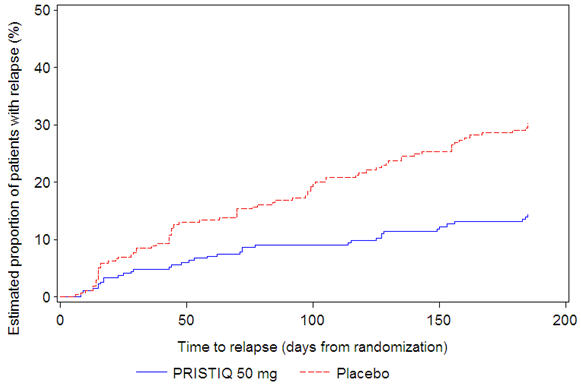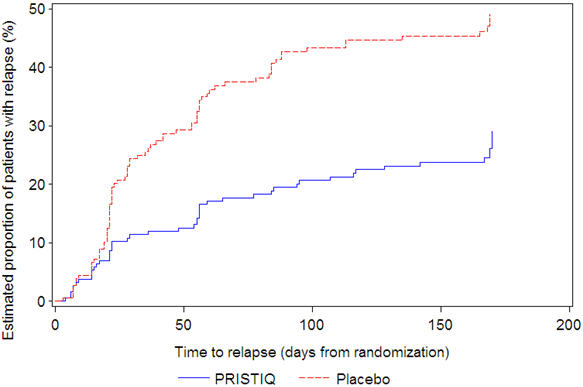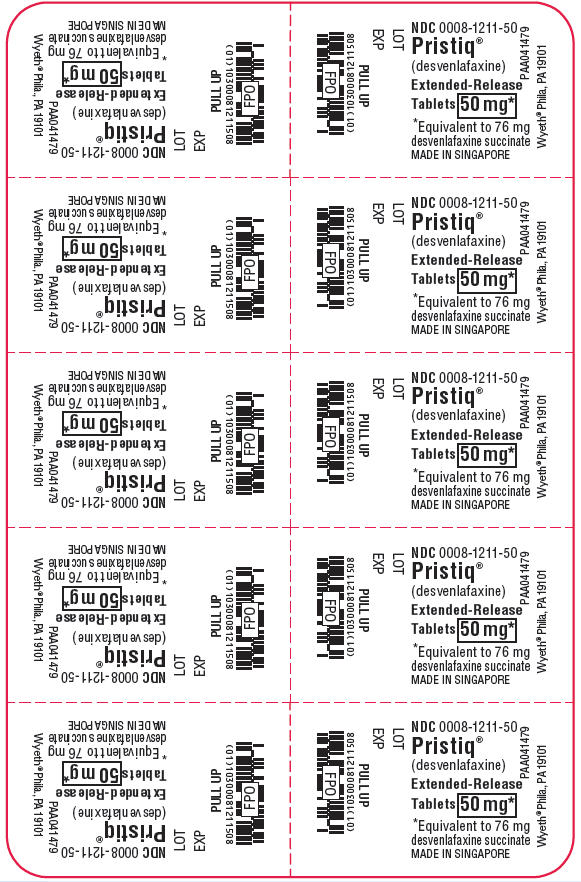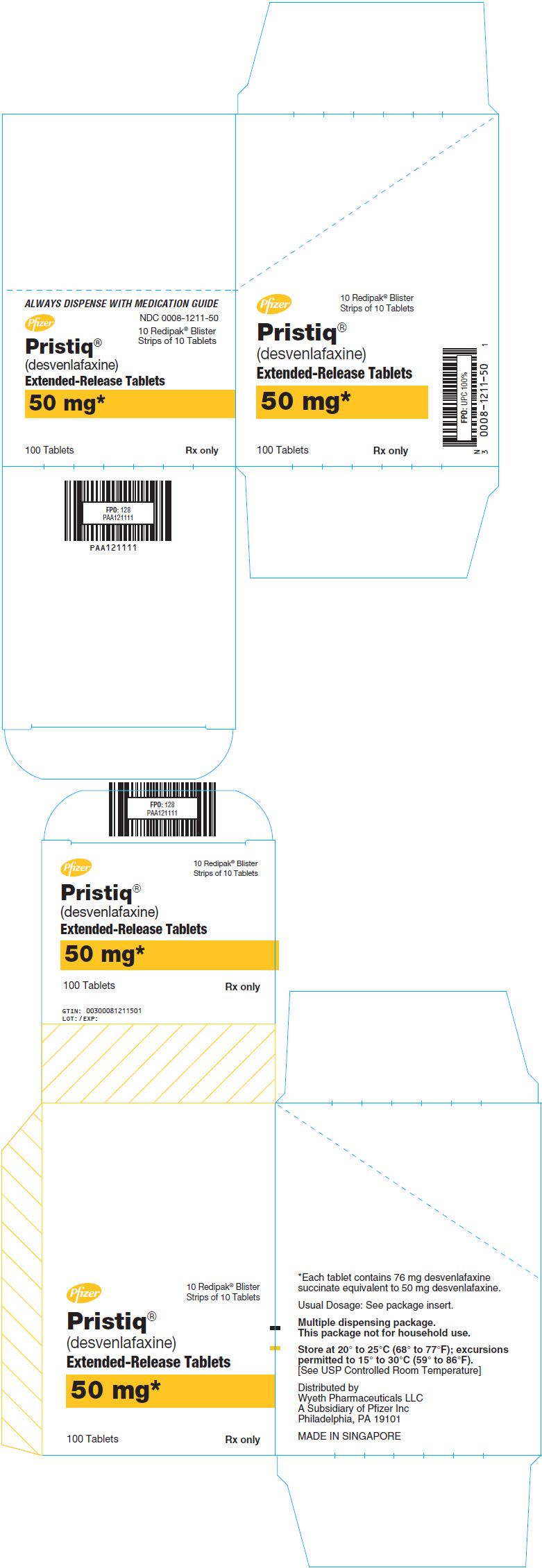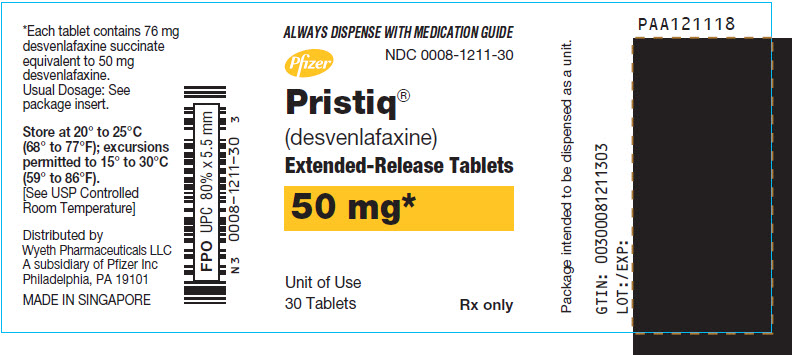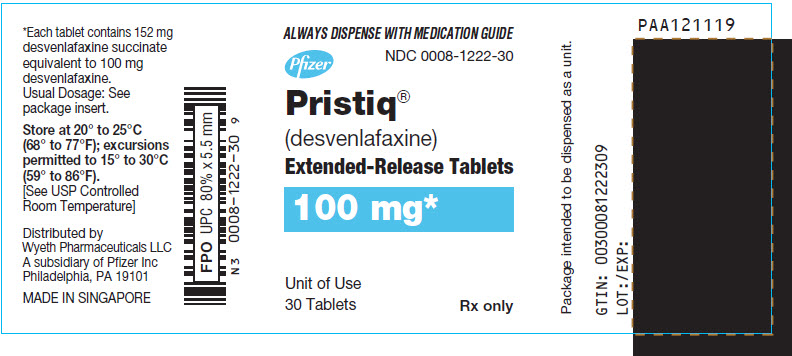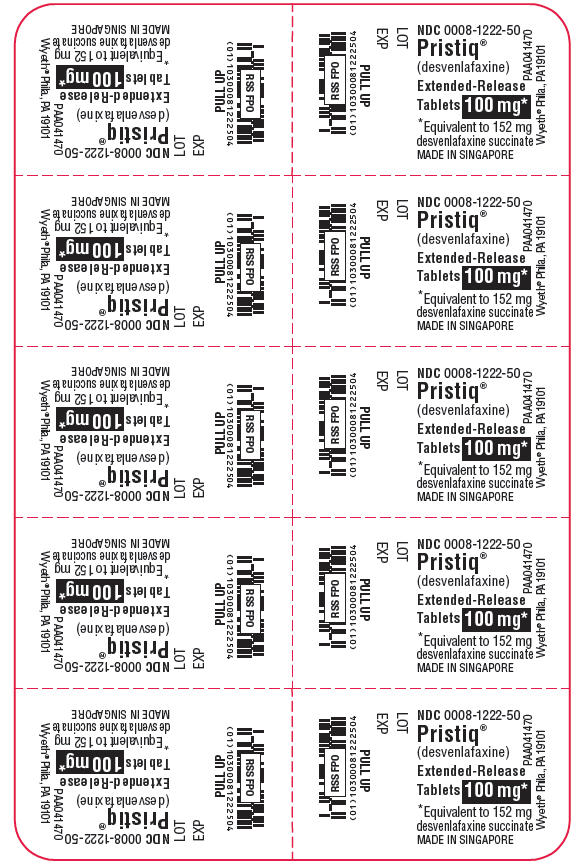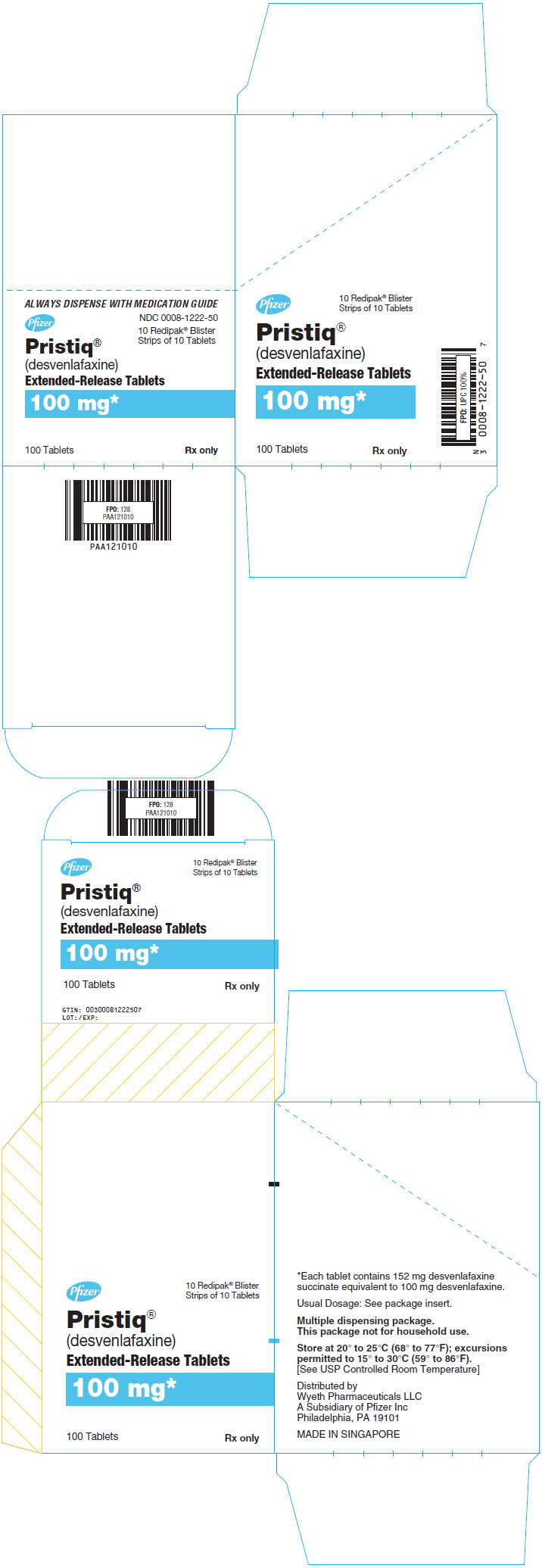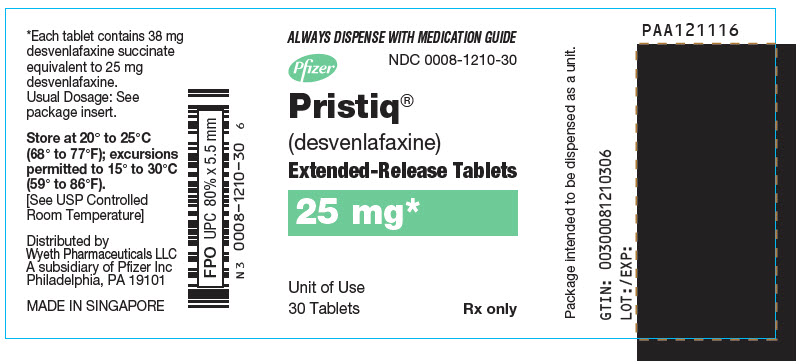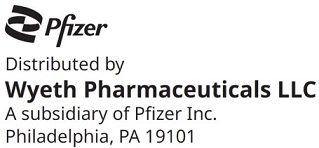 DRUG LABEL: Pristiq
NDC: 0008-1211 | Form: TABLET, EXTENDED RELEASE
Manufacturer: Wyeth Pharmaceuticals LLC, a subsidiary of Pfizer Inc.
Category: prescription | Type: HUMAN PRESCRIPTION DRUG LABEL
Date: 20251113

ACTIVE INGREDIENTS: DESVENLAFAXINE SUCCINATE 50 mg/1 1
INACTIVE INGREDIENTS: MICROCRYSTALLINE CELLULOSE; TALC; MAGNESIUM STEARATE; POLYETHYLENE GLYCOL, UNSPECIFIED; TITANIUM DIOXIDE; FERRIC OXIDE RED; POLYVINYL ALCOHOL, UNSPECIFIED; FERRIC OXIDE YELLOW; HYPROMELLOSE 2208 (15000 MPA.S)

HIGHLIGHTS OF PRESCRIBING INFORMATION

These highlights do not include all the information needed to use PRISTIQ safely and effectively. See full prescribing information for PRISTIQ.
PRISTIQ® (desvenlafaxine) Extended-Release Tablets, for oral use
Initial U.S. Approval: 2008

RECENT MAJOR CHANGES

Warnings and Precautions (5.2, 5.4) | 8/2023

WARNING: SUICIDAL THOUGHTS AND BEHAVIORS

See full prescribing information for complete boxed warning.

- Increased the risk of suicidal thoughts and behaviors in children, adolescents and young adults taking antidepressants (5.1).
- Closely monitor for clinical worsening and emergence of suicidal thoughts and behaviors (5.1).
- PRISTIQ is not approved for use in pediatric patients (8.4).

1 INDICATIONS AND USAGE

PRISTIQ is a serotonin and norepinephrine reuptake inhibitor (SNRI) indicated for the treatment of adults with major depressive disorder (MDD) (1).

2 DOSAGE AND ADMINISTRATION

- Recommended dose: 50 mg once daily with or without food (2.1).
- There was no evidence that doses greater than 50 mg per day confer any additional benefit (2.1).
- The 25 mg per day dose is intended for a gradual reduction in dose when discontinuing treatment or dosing in severe renal and end-stage renal disease patients (2.1).
- Discontinuation: Reduce dose gradually whenever possible (2.1).
- Take tablets whole; do not divide, crush, chew, or dissolve (2.1).
- Moderate renal impairment: Maximum dose 50 mg per day (2.2).
- Severe renal impairment and end-stage renal disease: Maximum dose 25 mg per day or 50 mg every other day (2.2).
- Moderate to severe hepatic impairment: Maximum dose 100 mg per day (2.3).

3 DOSAGE FORMS AND STRENGTHS

- PRISTIQ extended-release tablets: 25 mg, 50 mg and 100 mg (3).
- Each tablet contains 38 mg, 76 mg or 152 mg of desvenlafaxine succinate equivalent to 25 mg, 50 mg or 100 mg of desvenlafaxine, respectively (3).

4 CONTRAINDICATIONS

- Hypersensitivity to desvenlafaxine succinate, venlafaxine hydrochloride or any excipients in the PRISTIQ formulation (4).
- Serotonin Syndrome and MAOIs: Do not use MAOIs intended to treat psychiatric disorders with PRISTIQ or within 7 days of stopping treatment with PRISTIQ. Do not use PRISTIQ within 14 days of stopping an MAOI intended to treat psychiatric disorders. In addition, do not start PRISTIQ in a patient who is being treated with linezolid or intravenous methylene blue (4).

5 WARNINGS AND PRECAUTIONS

- Serotonin Syndrome: Increased risk when co-administered with other serotonergic agents, but also when taken alone. If it occurs, discontinue PRISTIQ and serotonergic agents and initiate supportive treatment (5.2).
- Elevated Blood Pressure: Control hypertension before initiating treatment. Monitor blood pressure regularly during treatment (5.3).
- Increased Risk of Bleeding: Concomitant use of aspirin, NSAIDs, other antiplatelet drugs, warfarin, and other anticoagulants may increase this risk (5.4).
- Angle Closure Glaucoma: Avoid use of antidepressants, including PRISTIQ, in patients with untreated anatomically narrow angles treated (5.5).
- Activation of Mania/Hypomania: Use cautiously in patients with Bipolar Disorder. Caution patients about risk of activation of mania/hypomania (5.6).
- Discontinuation Syndrome: Taper dose when possible and monitor for discontinuation symptoms (5.7).
- Seizure: Can occur. Use cautiously in patients with seizure disorder (5.8).
- Hyponatremia: Can occur in association with SIADH (5.9).
- Interstitial Lung Disease and Eosinophilic Pneumonia: Can occur (5.10).
- Sexual Dysfunction: PRISTIQ may cause symptoms of sexual dysfunction (5.11).

6 ADVERSE REACTIONS

Most common adverse reactions (incidence ≥5% and twice the rate of placebo in the 50 or 100 mg dose groups) were: nausea, dizziness, insomnia, hyperhidrosis, constipation, somnolence, decreased appetite, anxiety, and specific male sexual function disorders (6.1).

To report SUSPECTED ADVERSE REACTIONS, contact Wyeth Pharmaceuticals LLC, a subsidiary of Pfizer Inc., at 1-800-438-1985 or FDA at 1-800-FDA-1088 or www.fda.gov/medwatch.

8 USE IN SPECIFIC POPULATIONS

- Pregnancy: Third trimester use may result in neonatal discontinuation syndrome (8.1).
- Geriatric Use: There is an increased incidence of orthostatic hypotension in desvenlafaxine treated patients ≥ 65 years (6.1 and 8.5).

FULL PRESCRIBING INFORMATION

WARNING: SUICIDAL THOUGHTS AND BEHAVIORS

Antidepressants increased the risk of suicidal thoughts and behavior in children, adolescents, and young adults in short-term studies. These studies did not show an increase in the risk of suicidal thoughts and behavior with antidepressant use in patients over age 24; there was a reduction in risk with antidepressant use in patients aged 65 and older [see Warnings and Precautions (5.1)].

In patients of all ages who are started on antidepressant therapy, monitor closely for worsening, and for emergence of suicidal thoughts and behaviors. Advise families and caregivers of the need for close observation and communication with the prescriber [see Warnings and Precautions (5.1)].

PRISTIQ is not approved for use in pediatric patients [see Use in Specific Populations (8.4)].

1 INDICATIONS AND USAGE

PRISTIQ is indicated for the treatment of adults with major depressive disorder (MDD) [see Clinical Studies (14)].

2 DOSAGE AND ADMINISTRATION

2.1 General Instructions for Use

The recommended dose for PRISTIQ is 50 mg once daily, with or without food. The 50 mg dose is both a starting dose and the therapeutic dose. PRISTIQ should be taken at approximately the same time each day. Tablets must be swallowed whole with fluid and not divided, crushed, chewed, or dissolved.

In clinical studies, doses of 10 mg to 400 mg per day were studied. In clinical studies, doses of 50 mg to 400 mg per day were shown to be effective, although no additional benefit was demonstrated at doses greater than 50 mg per day and adverse reactions and discontinuations were more frequent at higher doses.

The 25 mg per day dose is intended for a gradual reduction in dose when discontinuing treatment. When discontinuing therapy, gradual dose reduction is recommended whenever possible to minimize discontinuation symptoms [see Dosage and Administration (2.5) and Warnings and Precautions (5.7)].

2.2 Dosage Recommendations for Patients with Renal Impairment

The maximum recommended dose in patients with moderate renal impairment (24-hr creatinine clearance [ClCr] = 30 to 50 mL/min, Cockcroft-Gault [C-G]) is 50 mg per day. The maximum recommended dose in patients with severe renal impairment (ClCr 15 to 29 mL/min, C-G) or end-stage renal disease (ESRD, ClCr < 15 mL/min, C-G) is 25 mg every day or 50 mg every other day. Supplemental doses should not be given to patients after dialysis [see Use in Specific Populations (8.6) and Clinical Pharmacology (12.3)].

2.3 Dosage Recommendations for Patients with Hepatic Impairment

The recommended dose in patients with moderate to severe hepatic impairment (Child-Pugh score 7 to 15) is 50 mg per day. Dose escalation above 100 mg per day is not recommended [see Use in Specific Populations (8.7) and Clinical Pharmacology (12.3)].

2.4 Maintenance/Continuation/Extended Treatment

It is generally agreed that acute episodes of major depressive disorder require several months or longer of sustained pharmacologic therapy. Longer-term efficacy of PRISTIQ (50–400 mg) was established in two maintenance trials [see Clinical Studies (14)]. Patients should be periodically reassessed to determine the need for continued treatment.

2.5 Discontinuing PRISTIQ

Adverse reactions may occur upon discontinuation of PRISTIQ [see Warnings and Precautions (5.7)]. Gradually reduce the dosage rather than stopping PRISTIQ abruptly when discontinuing therapy with PRISTIQ. In some patients, discontinuation may need to occur over a period of several months.

2.6 Switching Patients From Other Antidepressants to PRISTIQ

Discontinuation symptoms have been reported when switching patients from other antidepressants, including venlafaxine, to PRISTIQ. Tapering of the initial antidepressant may be necessary to minimize discontinuation symptoms.

2.7 Switching Patients to or from a Monoamine Oxidase Inhibitor (MAOI) Intended to Treat Psychiatric Disorders

At least 14 days should elapse between discontinuation of an MAOI intended to treat psychiatric disorders and initiation of therapy with PRISTIQ. Conversely, at least 7 days should be allowed after stopping PRISTIQ before starting an MAOI intended to treat psychiatric disorders [see Contraindications (4)].

2.8 Use of PRISTIQ with other MAOIs such as Linezolid or Methylene Blue

Do not start PRISTIQ in a patient who is being treated with linezolid or intravenous methylene blue because there is increased risk of serotonin syndrome. In a patient who requires more urgent treatment of a psychiatric condition, other interventions, including hospitalization, should be considered [see Contraindications (4)].

In some cases, a patient already receiving PRISTIQ therapy may require urgent treatment with linezolid or intravenous methylene blue. If acceptable alternatives to linezolid or intravenous methylene blue treatment are not available and the potential benefits of linezolid or intravenous methylene blue treatment are judged to outweigh the risks of serotonin syndrome in a particular patient, PRISTIQ should be stopped promptly, and linezolid or intravenous methylene blue can be administered. The patient should be monitored for symptoms of serotonin syndrome for 7 days or until 24 hours after the last dose of linezolid or intravenous methylene blue, whichever comes first. Therapy with PRISTIQ may be resumed 24 hours after the last dose of linezolid or intravenous methylene blue [see Warnings and Precautions (5.2)].

The risk of administering methylene blue by non-intravenous routes (such as oral tablets or by local injection) or in intravenous doses much lower than 1 mg/kg with PRISTIQ is unclear. The clinician should, nevertheless, be aware of the possibility of emergent symptoms of serotonin syndrome with such use [see Warnings and Precautions (5.2)].

3 DOSAGE FORMS AND STRENGTHS

- 25 mg Tablet: tan, square pyramid tablet debossed with "W" over "25" on the flat side
- 50 mg Tablet: light pink, square pyramid tablet debossed with "W" over "50" on the flat side
- 100 mg Tablet: reddish-orange, square pyramid tablet debossed with "W" over "100" on the flat side

4 CONTRAINDICATIONS

- Hypersensitivity to desvenlafaxine succinate, venlafaxine hydrochloride or to any excipients in the PRISTIQ formulation. Angioedema has been reported in patients treated with PRISTIQ [see Adverse Reactions (6.1)].
- The use of MAOIs intended to treat psychiatric disorders with PRISTIQ or within 7 days of stopping treatment with PRISTIQ is contraindicated because of an increased risk of serotonin syndrome. The use of PRISTIQ within 14 days of stopping an MAOI intended to treat psychiatric disorders is also contraindicated [see Dosage and Administration (2.7) and Warnings and Precautions (5.2)].
- Starting PRISTIQ in a patient who is being treated with MAOIs such as linezolid or intravenous methylene blue is also contraindicated because of an increased risk of serotonin syndrome [see Dosage and Administration (2.8) and Warnings and Precautions (5.2)].

5 WARNINGS AND PRECAUTIONS

5.1 Suicidal Thoughts and Behaviors in Pediatric and Young Adult Patients

Patients with MDD, both adult and pediatric, may experience worsening of their depression and/or the emergence of suicidal ideation and behavior (suicidality) or unusual changes in behavior, whether or not they are taking antidepressant medications, and this risk may persist until significant remission occurs. Suicide is a known risk of depression and certain other psychiatric disorders, and these disorders themselves are the strongest predictors of suicide. There has been a long-standing concern, however, that antidepressants may have a role in inducing worsening of depression and the emergence of suicidality in certain patients during the early phases of treatment. Pooled analyses of short-term placebo-controlled studies of antidepressant drugs (SSRIs and others) showed that these drugs increase the risk of suicidal thinking and behavior (suicidality) in children, adolescents, and young adults (ages 18 to 24) with major depressive disorder (MDD) and other psychiatric disorders. Short-term studies did not show an increase in the risk of suicidality with antidepressants compared to placebo in adults beyond age 24; there was a reduction with antidepressants compared to placebo in adults aged 65 and older.

The pooled analyses of placebo-controlled studies in children and adolescents with MDD, obsessive compulsive disorder (OCD), or other psychiatric disorders included a total of 24 short-term studies of 9 antidepressant drugs in over 4,400 patients. The pooled analyses of placebo-controlled studies in adults with MDD or other psychiatric disorders included a total of 295 short-term studies (median duration of 2 months) of 11 antidepressant drugs in over 77,000 patients. There was considerable variation in risk of suicidality among drugs, but a tendency toward an increase in the younger patients for almost all drugs studied. There were differences in absolute risk of suicidality across the different indications, with the highest incidence in MDD. The risk differences (drug vs. placebo), however, were relatively stable within age strata and across indications. These risk differences (drug-placebo difference in the number of cases of suicidality per 1,000 patients treated) are provided in Table 1.

Table 1
Age Range | Drug-Placebo Difference in Number of Cases of Suicidality per 1,000 Patients Treated
 | Increases Compared to Placebo
<18 | 14 additional cases
18 to 24 | 5 additional cases
 | Decreases Compared to Placebo
25 to 64 | 1 fewer case
≥65 | 6 fewer cases

No suicides occurred in any of the pediatric studies. There were suicides in the adult studies, but the number was not sufficient to reach any conclusion about drug effect on suicide.

It is unknown whether the suicidality risk extends to longer-term use, i.e., beyond several months. However, there is substantial evidence from placebo-controlled maintenance studies in adults with depression that the use of antidepressants can delay the recurrence of depression.

All patients being treated with antidepressants for any indication should be monitored appropriately and observed closely for clinical worsening, suicidality, and unusual changes in behavior, especially during the initial few months of a course of drug therapy, or at times of dose changes, either increases or decreases.

The following symptoms, anxiety, agitation, panic attacks, insomnia, irritability, hostility, aggressiveness, impulsivity, akathisia (psychomotor restlessness), hypomania, and mania, have been reported in adult and pediatric patients being treated with antidepressants for major depressive disorder as well as for other indications, both psychiatric and nonpsychiatric. Although a causal link between the emergence of such symptoms and either the worsening of depression and/or the emergence of suicidal impulses has not been established, there is concern that such symptoms may represent precursors to emerging suicidality.

Consideration should be given to changing the therapeutic regimen, including possibly discontinuing the medication, in patients whose depression is persistently worse, or who are experiencing emergent suicidality or symptoms that might be precursors to worsening depression or suicidality, especially if these symptoms are severe, abrupt in onset, or were not part of the patient's presenting symptoms.

If the decision has been made to discontinue treatment, medication should be tapered, as rapidly as is feasible, but with recognition that abrupt discontinuation can be associated with certain symptoms [see Dosage and Administration (2.4), Warnings and Precautions (5.7)].

Families and caregivers of patients being treated with antidepressants for major depressive disorder or other indications, both psychiatric and nonpsychiatric, should be alerted about the need to monitor patients for the emergence of agitation, irritability, unusual changes in behavior, and the other symptoms described above, as well as the emergence of suicidality, and to report such symptoms immediately to healthcare providers. Such monitoring should include daily observation by families and caregivers.

Prescriptions for PRISTIQ should be written for the smallest quantity of tablets consistent with good patient management, in order to reduce the risk of overdose.

Screening Patients for Bipolar Disorder

A major depressive episode may be the initial presentation of bipolar disorder. It is generally believed (though not established in controlled studies) that treating such an episode with an antidepressant alone may increase the likelihood of precipitation of a mixed/manic episode in patients at risk for bipolar disorder. Whether any of the symptoms described above represent such a conversion is unknown. However, prior to initiating treatment with an antidepressant, patients with depressive symptoms should be adequately screened to determine if they are at risk for bipolar disorder; such screening should include a detailed psychiatric history, including a family history of suicide, bipolar disorder, and depression. It should be noted that PRISTIQ is not approved for use in treating bipolar depression.

5.2 Serotonin Syndrome

Serotonin-norepinephrine reuptake inhibitors (SNRIs) and selective-serotonin reuptake inhibitors (SSRIs), including PRISTIQ, can precipitate serotonin syndrome, a potentially life-threatening condition. The risk is increased with concomitant use of other serotonergic drugs (including triptans, tricyclic antidepressants, fentanyl, lithium, tramadol, meperidine, methadone, tryptophan, buspirone, amphetamines, and St. John's Wort) and with drugs that impair metabolism of serotonin, i.e., MAOIs [see Contraindications (4), Drug Interactions (7.1)]. Serotonin syndrome can also occur when these drugs are used alone.

Serotonin syndrome signs and symptoms may include mental status changes (e.g., agitation, hallucinations, delirium, and coma), autonomic instability (e.g., tachycardia, labile blood pressure, dizziness, diaphoresis, flushing, hyperthermia), neuromuscular symptoms (e.g., tremor, rigidity, myoclonus, hyperreflexia, incoordination), seizures, and gastrointestinal symptoms (e.g., nausea, vomiting, diarrhea).

The concomitant use of PRISTIQ with MAOIs is contraindicated. In addition, do not initiate PRISTIQ in a patient being treated with MAOIs such as linezolid or intravenous methylene blue. No reports involved the administration of methylene blue by other routes (such as oral tablets or local tissue injection). If it is necessary to initiate treatment with an MAOI such as linezolid or intravenous methylene blue in a patient taking PRISTIQ, discontinue PRISTIQ before initiating treatment with the MAOI [see Contraindications (4), Drug Interactions (7.1)].

Monitor all patients taking PRISTIQ for the emergence of serotonin syndrome. Discontinue treatment with PRISTIQ and any concomitant serotonergic agents immediately if the above symptoms occur, and initiate supportive symptomatic treatment. If concomitant use of PRISTIQ with other serotonergic drugs is clinically warranted, inform patients of the increased risk for serotonin syndrome and monitor for symptoms.

5.3 Elevated Blood Pressure

Patients receiving PRISTIQ should have regular monitoring of blood pressure since increases in blood pressure were observed in clinical studies [see Adverse Reactions (6.1)]. Pre-existing hypertension should be controlled before initiating treatment with PRISTIQ. Caution should be exercised in treating patients with pre-existing hypertension, cardiovascular, or cerebrovascular conditions that might be compromised by increases in blood pressure. Cases of elevated blood pressure requiring immediate treatment have been reported with PRISTIQ.

Sustained blood pressure increases could have adverse consequences. For patients who experience a sustained increase in blood pressure while receiving PRISTIQ, either dose reduction or discontinuation should be considered [see Adverse Reactions (6.1)].

5.4 Increased Risk of Bleeding

Drugs that interfere with serotonin reuptake inhibition, including PRISTIQ, may increase the risk of bleeding events. Concomitant use of aspirin, nonsteroidal anti-inflammatory drugs, warfarin, and other anticoagulants may add to this risk. Case reports and epidemiological studies (case-control and cohort design) have demonstrated an association between use of drugs that interfere with serotonin reuptake and the occurrence of gastrointestinal bleeding. Based on data from the published observational studies, exposure to SNRIs, particularly in the month before delivery, has been associated with a less than 2-fold increase in the risk of postpartum hemorrhage [see Use in Specific Populations (8.1)]. Bleeding events related to SSRIs and SNRIs have ranged from ecchymosis, hematoma, epistaxis, and petechiae to life-threatening hemorrhages.

Inform patients about the increased risk of bleeding associated with the concomitant use of PRISTIQ and antiplatelet agents or anticoagulants. For patients taking warfarin, carefully monitor coagulation indices when initiating, titrating, or discontinuing PRISTIQ.

5.5 Angle Closure Glaucoma

The pupillary dilation that occurs following use of many antidepressant drugs including PRISTIQ may trigger an angle closure attack in a patient with anatomically narrow angles who does not have a patent iridectomy. Avoid use of antidepressants, including PRISTIQ, in patients with untreated anatomically narrow angles.

5.6 Activation of Mania/Hypomania

During all MDD phase 2 and phase 3 studies, mania was reported for approximately 0.02% of patients treated with PRISTIQ. Activation of mania/hypomania has also been reported in a small proportion of patients with major affective disorder who were treated with other marketed antidepressants. As with all antidepressants, PRISTIQ should be used cautiously in patients with a history or family history of mania or hypomania.

5.7 Discontinuation Syndrome

Adverse reactions after discontinuation of serotonergic antidepressants, particularly after abrupt discontinuation, include: nausea, sweating, dysphoric mood, irritability, agitation, dizziness, sensory disturbances (e.g., paresthesia, such as electric shock sensations), tremor, anxiety, confusion, headache, lethargy, emotional lability, insomnia, hypomania, tinnitus, and seizures [see Adverse Reactions (6.1)].

There have been postmarketing reports of serious discontinuation symptoms with PRISTIQ, which can be protracted and severe. Completed suicide, suicidal thoughts, and severe aggression (including hostility, rage, and homicidal ideation) have been observed in patients during reduction in PRISTIQ dosage, including during discontinuation. Other postmarketing reports describe visual changes (such as blurred vision or trouble focusing) and increased blood pressure after stopping or reducing the dose of PRISTIQ.

Patients should be monitored when discontinuing treatment with PRISTIQ. A gradual reduction in the dose, rather than abrupt cessation, is recommended. If intolerable symptoms occur following a decrease in the dose or upon discontinuation of treatment, then resuming the previously prescribed dose may be considered. Subsequently, the healthcare provider may continue decreasing the dose, but at a more gradual rate. In some patients, discontinuation may need to occur over a period of several months [see Dosage and Administration (2.5)].

5.8 Seizure

Cases of seizure have been reported in pre-marketing clinical studies with PRISTIQ. PRISTIQ has not been systematically evaluated in patients with a seizure disorder. Patients with a history of seizures were excluded from pre-marketing clinical studies. PRISTIQ should be prescribed with caution in patients with a seizure disorder.

5.9 Hyponatremia

Hyponatremia may occur as a result of treatment with SSRIs and SNRIs, including PRISTIQ. In many cases, this hyponatremia appears to be the result of the syndrome of inappropriate antidiuretic hormone secretion (SIADH). Cases with serum sodium lower than 110 mmol/L have been reported. Elderly patients may be at greater risk of developing hyponatremia with SSRIs and SNRIs. Also, patients taking diuretics or who are otherwise volume depleted can be at greater risk [see Use in Specific Populations (8.5) and Clinical Pharmacology (12.3)]. Discontinuation of PRISTIQ should be considered in patients with symptomatic hyponatremia and appropriate medical intervention should be instituted.

Signs and symptoms of hyponatremia include headache, difficulty concentrating, memory impairment, confusion, weakness, and unsteadiness, which can lead to falls. Signs and symptoms associated with more severe and/or acute cases have included hallucination, syncope, seizure, coma, respiratory arrest, and death.

5.10 Interstitial Lung Disease and Eosinophilic Pneumonia

Interstitial lung disease and eosinophilic pneumonia associated with venlafaxine (the parent drug of PRISTIQ) therapy have been rarely reported. The possibility of these adverse events should be considered in patients treated with PRISTIQ who present with progressive dyspnea, cough, or chest discomfort. Such patients should undergo a prompt medical evaluation, and discontinuation of PRISTIQ should be considered.

5.11 Sexual Dysfunction

Use of SNRIs, including PRISTIQ, may cause symptoms of sexual dysfunction [see Adverse Reactions (6.1)]. In male patients, SNRI use may result in ejaculatory delay or failure, decreased libido, and erectile dysfunction. In female patients, SNRI use may result in decreased libido and delayed or absent orgasm.

It is important for prescribers to inquire about sexual function prior to initiation of PRISTIQ and to inquire specifically about changes in sexual function during treatment, because sexual function may not be spontaneously reported. When evaluating changes in sexual function, obtaining a detailed history (including timing of symptom onset) is important because sexual symptoms may have other causes, including the underlying psychiatric disorder. Discuss potential management strategies to support patients in making informed decisions about treatment.

6 ADVERSE REACTIONS

The following adverse reactions are discussed in greater detail in other sections of the label.

- Hypersensitivity [see Contraindications (4)]
- Suicidal Thoughts and Behaviors in Pediatric and Young Adult Patients [see Warnings and Precautions (5.1)]
- Serotonin Syndrome [see Warnings and Precautions (5.2)]
- Elevated Blood Pressure [see Warnings and Precautions (5.3)]
- Increased Risk of Bleeding [see Warnings and Precautions (5.4)]
- Angle Closure Glaucoma [see Warnings and Precautions (5.5)]
- Activation of Mania/Hypomania [see Warnings and Precautions (5.6)]
- Discontinuation Syndrome [see Warnings and Precautions (5.7)]
- Seizure [see Warnings and Precautions (5.8)]
- Hyponatremia [see Warnings and Precautions (5.9)]
- Interstitial Lung Disease and Eosinophilic Pneumonia [see Warnings and Precautions (5.10)]
- Sexual Dysfunction [see Warnings and Precautions (5.11)]

6.1 Clinical Studies Experience

Because clinical trials are conducted under widely varying conditions, adverse reaction rates observed in the clinical trials of a drug cannot be directly compared to rates in the clinical studies of another drug and may not reflect the rates observed in clinical practice.

Patient Exposure

PRISTIQ was evaluated for safety in 8,394 patients diagnosed with major depressive disorder who participated in multiple-dose pre-marketing studies, representing 2,784 patient-years of exposure. Of the total 8,394 patients exposed to at least one dose of PRISTIQ; 2,116 were exposed to PRISTIQ for 6 months, representing 1,658 patient-years of exposure, and 421 were exposed for one year, representing 416 patient-years of exposure.

Adverse Reactions Reported as Reasons for Discontinuation of Treatment

In the pre-marketing pooled 8-week placebo-controlled studies in patients with MDD, 1,834 patients were exposed to PRISTIQ (50 to 400 mg). Of the 1,834 patients, 12% discontinued treatment due to an adverse reaction, compared with 3% of the 1,116 placebo-treated patients. At the recommended dose of 50 mg, the discontinuation rate due to an adverse reaction for PRISTIQ (4.1%) was similar to the rate for placebo (3.8%). For the 100 mg dose of PRISTIQ the discontinuation rate due to an adverse reaction was 8.7%.

The most common adverse reactions leading to discontinuation in at least 2% and at a rate greater than placebo of the PRISTIQ treated patients in the short-term studies, up to 8 weeks, were: nausea (4%); dizziness, headache and vomiting (2% each). In a longer-term study, up to 9 months, the most common was vomiting (2%).

Common Adverse Reactions in Placebo-Controlled MDD Studies

The most commonly observed adverse reactions in PRISTIQ treated MDD patients in pre-marketing pooled 8-week, placebo-controlled, fixed-dose studies (incidence ≥ 5% and at least twice the rate of placebo in the 50 or 100 mg dose groups) were: nausea, dizziness, insomnia, hyperhidrosis, constipation, somnolence, decreased appetite, anxiety, and specific male sexual function disorders.

Table 2 shows the incidence of common adverse reactions that occurred in ≥ 2% of PRISTIQ treated MDD patients and twice the rate of placebo at any dose in the pre-marketing pooled 8-week, placebo-controlled, fixed dose clinical studies.

Table 2: Common Adverse Reactions (≥ 2% in any Fixed-Dose Group and Twice the Rate of Placebo) in Pre-marketing Pooled MDD 8-Week Placebo-Controlled Studies
 | Percentage of Patients Reporting Reaction
 |  | PRISTIQ
System Organ Class Preferred Term | Placebo (n=636) | 50 mg (n=317) | 100 mg (n=424) | 200 mg (n=307) | 400 mg (n=317)
Cardiac disorders
Blood pressure increased | 1 | 1 | 1 | 2 | 2
Gastrointestinal disorders
Nausea | 10 | 22 | 26 | 36 | 41
Dry mouth | 9 | 11 | 17 | 21 | 25
Constipation | 4 | 9 | 9 | 10 | 14
Vomiting | 3 | 3 | 4 | 6 | 9
General disorders and administration site conditions
Fatigue | 4 | 7 | 7 | 10 | 11
Chills | 1 | 1 | <1 | 3 | 4
Feeling jittery | 1 | 1 | 2 | 3 | 3
Metabolism and nutrition disorders
Decreased appetite | 2 | 5 | 8 | 10 | 10
Nervous system disorders
Dizziness | 5 | 13 | 10 | 15 | 16
Somnolence | 4 | 4 | 9 | 12 | 12
Tremor | 2 | 2 | 3 | 9 | 9
Disturbance in attention | <1 | <1 | 1 | 2 | 1
Psychiatric disorders
Insomnia | 6 | 9 | 12 | 14 | 15
Anxiety | 2 | 3 | 5 | 4 | 4
Nervousness | 1 | <1 | 1 | 2 | 2
Abnormal dreams | 1 | 2 | 3 | 2 | 4
Renal and urinary disorders
Urinary hesitation | 0 | <1 | 1 | 2 | 2
Respiratory, thoracic and mediastinal disorders
Yawning | <1 | 1 | 1 | 4 | 3
Skin and subcutaneous tissue disorders
Hyperhidrosis | 4 | 10 | 11 | 18 | 21
Special Senses
Vision blurred | 1 | 3 | 4 | 4 | 4
Mydriasis | <1 | 2 | 2 | 6 | 6
Vertigo | 1 | 2 | 1 | 5 | 3
Tinnitus | 1 | 2 | 1 | 1 | 2
Dysgeusia | 1 | 1 | 1 | 1 | 2
Vascular disorders
Hot flush | <1 | 1 | 1 | 2 | 2

Sexual Function Adverse Reactions

Table 3 shows the incidence of sexual function adverse reactions that occurred in ≥ 2% of PRISTIQ treated MDD patients in any fixed-dose group (pre-marketing pooled 8-week, placebo-controlled, fixed -dose, clinical studies) [see Warnings and Precautions (5.11)].

Table 3: Sexual Function Adverse Reactions (≥ 2% in Men or Women in any PRISTIQ Group) During the On-Therapy Period
 |  | PRISTIQ
 | Placebo (n=239) | 50 mg (n=108) | 100 mg (n=157) | 200 mg (n=131) | 400 mg (n=154)
Men only
Anorgasmia | 0 | 0 | 3 | 5 | 8
Libido decreased | 1 | 4 | 5 | 6 | 3
Orgasm abnormal | 0 | 0 | 1 | 2 | 3
Ejaculation delayed | <1 | 1 | 5 | 7 | 6
Erectile dysfunction | 1 | 3 | 6 | 8 | 11
Ejaculation disorder | 0 | 0 | 1 | 2 | 5
Ejaculation failure | 0 | 1 | 0 | 2 | 2
Sexual dysfunction | 0 | 1 | 0 | 0 | 2
 |  | PRISTIQ
 | Placebo (n=397) | 50 mg (n=209) | 100 mg (n=267) | 200 mg (n=176) | 400 mg (n=163)
Women only
Anorgasmia | 0 | 1 | 1 | 0 | 3

Other Adverse Reactions Observed in Premarketing and Postmarketing Clinical Studies

Other infrequent adverse reactions, not described elsewhere in the label, occurring at an incidence of < 2% in MDD patients treated with PRISTIQ were:

Cardiac disorders – Tachycardia.

General disorders and administration site conditions – Asthenia.

Investigations – Weight increased, liver function test abnormal, blood prolactin increased.

Musculoskeletal and connective tissue disorders – Musculoskeletal stiffness.

Nervous system disorders –Syncope, convulsion, dystonia.

Psychiatric disorders – Depersonalization, bruxism.

Renal and urinary disorders – Urinary retention.

Skin and subcutaneous tissue disorders – Rash, alopecia, photosensitivity reaction, angioedema.

In clinical studies, there were uncommon reports of ischemic cardiac adverse reactions, including myocardial ischemia, myocardial infarction, and coronary occlusion requiring revascularization; these patients had multiple underlying cardiac risk factors. More patients experienced these events during PRISTIQ treatment as compared to placebo.

Laboratory, ECG and Vital Sign Changes Observed in MDD Clinical Studies

The following changes were observed in pre-marketing placebo-controlled, short-term MDD studies with PRISTIQ.

Lipids

Elevations in fasting serum total cholesterol, LDL (low density lipoproteins) cholesterol, and triglycerides occurred in the controlled studies. Some of these abnormalities were considered potentially clinically significant.

The percentage of patients who exceeded a predetermined threshold value is shown in Table 4.

Table 4: Incidence (%) of Patients With Lipid Abnormalities of Potential Clinical Significance*
 |  | PRISTIQ
 | Placebo | 50 mg | 100 mg | 200 mg | 400 mg
Total Cholesterol *(Increase of ≥ 50 mg/dl and an absolute value of ≥ 261 mg/dl) | 2 | 3 | 4 | 4 | 10
LDL Cholesterol *(Increase ≥ 50 mg/dl and an absolute value of ≥ 190 mg/dl) | 0 | 1 | 0 | 1 | 2
Triglycerides, fasting *(Fasting: ≥ 327 mg/dl) | 3 | 2 | 1 | 4 | 6

Proteinuria

Proteinuria, greater than or equal to trace, was observed in the pre-marketing fixed-dose controlled studies (see Table 5). This proteinuria was not associated with increases in BUN or creatinine and was generally transient.

Table 5: Incidence (%) of Patients with Proteinuria in the Fixed-dose Clinical Studies
 |  | PRISTIQ
 | Placebo | 50 mg | 100 mg | 200 mg | 400 mg
Proteinuria | 4 | 6 | 8 | 5 | 7

Vital Sign Changes

Table 6 summarizes the changes that were observed in placebo-controlled, short-term, pre-marketing studies with PRISTIQ in patients with MDD (doses 50 to 400 mg).

Table 6: Mean Changes in Vital Signs at Final on Therapy for All Short-term, Fixed-dose Controlled Studies
 |  | PRISTIQ
 | Placebo | 50 mg | 100 mg | 200 mg | 400 mg
Blood pressure
Supine systolic bp (mm Hg) | -1.4 | 1.2 | 2.0 | 2.5 | 2.1
Supine diastolic bp (mm Hg) | -0.6 | 0.7 | 0.8 | 1.8 | 2.3
Pulse rate
Supine pulse (bpm) | -0.3 | 1.3 | 1.3 | 0.9 | 4.1
Weight (kg) | 0.0 | -0.4 | -0.6 | -0.9 | -1.1

Treatment with PRISTIQ at all doses from 50 mg per day to 400 mg per day in controlled studies was associated with sustained hypertension, defined as treatment-emergent supine diastolic blood pressure (SDBP) ≥90 mm Hg and ≥10 mm Hg above baseline for 3 consecutive on-therapy visits (see Table 7). Analyses of patients in PRISTIQ pre-marketing short-term controlled studies who met criteria for sustained hypertension revealed a consistent increase in the proportion of patients who developed sustained hypertension. This was seen at all doses with a suggestion of a higher rate at 400 mg per day.

Table 7: Proportion of Patients with Sustained Elevation of Supine Diastolic Blood Pressure
Treatment Group | Proportion of Patients with Sustained Hypertension
Placebo | 0.5%
PRISTIQ 50 mg per day | 1.3%
PRISTIQ 100 mg per day | 0.7%
PRISTIQ 200 mg per day | 1.1%
PRISTIQ 400 mg per day | 2.3%

Orthostatic Hypotension

In the pre-marketing short-term, placebo-controlled clinical studies with doses of 50 to 400 mg, systolic orthostatic hypotension (decrease ≥30 mm Hg from supine to standing position) occurred more frequently in patients ≥65 years of age receiving PRISTIQ (8%, 7/87) versus placebo (2.5%, 1/40), compared to patients <65 years of age receiving PRISTIQ (0.9%, 18/1,937) versus placebo (0.7%, 8/1,218).

6.2 Postmarketing Experience

The following adverse reaction has been identified during post-approval use of PRISTIQ. Because these reactions are reported voluntarily from a population of uncertain size, it is not always possible to reliably estimate their frequency or establish a causal relationship to drug exposure:

Skin and subcutaneous tissue disorders – Stevens-Johnson syndrome

Gastrointestinal disorders – Pancreatitis acute

Cardiovascular system – Takotsubo cardiomyopathy

Respiratory, thoracic and mediastinal disorders - Anosmia, hyposmia

7 DRUG INTERACTIONS

7.1 Drugs Having Clinically Important Interactions with PRISTIQ

Table 8: Clinically Important Drug Interactions with PRISTIQ
Monoamine Oxidase Inhibitors (MAOI)
Clinical Impact | The concomitant use of SSRIs and SNRIs including PRISTIQ with MAOIs increases the risk of serotonin syndrome.
Intervention | Concomitant use of PRISTIQ is contraindicated:; - With an MAOI intended to treat psychiatric disorders or within 7 days of stopping treatment with PRISTIQ. - Within 14 days of stopping an MAOI intended to treat psychiatric disorders. - In a patient who is being treated with linezolid or intravenous methylene blue.; [see Dosage and Administration (2.7), Contraindications (4) and Warnings and Precautions (5.2)].
Examples | selegiline, tranylcypromine, isocarboxazid, phenelzine, linezolid, methylene blue
Other Serotonergic Drugs
Clinical Impact | Concomitant use of PRISTIQ with other serotonergic drugs increases the risk of serotonin syndrome.
Intervention | Monitor for symptoms of serotonin syndrome when PRISTIQ is used concomitantly with other drugs that may affect the serotonergic neurotransmitter systems. If serotonin syndrome occurs, consider discontinuation of PRISTIQ and/or concomitant serotonergic drugs [see Warnings and Precautions (5.2)].
Examples | other SNRIs, SSRIs, triptans, tricyclic antidepressants, opioids, lithium, buspirone, amphetamines, tryptophan, and St. John's Wort
Drugs that Interfere with Hemostasis
Clinical Impact | Concomitant use of PRISTIQ with an antiplatelet or anticoagulant drug may potentiate the risk of bleeding. This may be due to the effect of PRISTIQ on the release of serotonin by platelets.
Intervention | Closely monitor for bleeding for patients receiving an antiplatelet or anticoagulant drug when PRISTIQ is initiated or discontinued [see Warnings and Precautions (5.4)].
Examples | NSAIDs, aspirin, and warfarin
Drugs that are Primarily Metabolized by CYP2D6
Clinical Impact | Concomitant use of PRISTIQ increases Cmax and AUC of a drug primarily metabolized by CYP2D6 which may increase the risk of toxicity of the CYP2D6 substrate drug [see Clinical Pharmacology (12.3)].
Intervention | Original dose should be taken when co-administered with PRISTIQ 100 mg or lower. Reduce the dose of these drugs by up to one-half if co-administered with 400 mg of PRISTIQ.
Examples | desipramine, atomoxetine, dextromethorphan, metoprolol, nebivolol, perphenazine, tolterodine

7.2 Drugs Having No Clinically Important Interactions with PRISTIQ

Based on pharmacokinetic studies, no dosage adjustment is required for drugs that are mainly metabolized by CYP3A4 (e.g., midazolam), or for drugs that are metabolized by both CYP2D6 and CYP3A4 (e.g., tamoxifen, aripiprazole), when administered concomitantly with PRISTIQ [see Clinical Pharmacology (12.3)].

7.3 Alcohol

A clinical study has shown that PRISTIQ does not increase the impairment of mental and motor skills caused by ethanol. However, as with all CNS-active drugs, patients should be advised to avoid alcohol consumption while taking PRISTIQ.

7.4 Drug-Laboratory Test Interactions

False-positive urine immunoassay screening tests for phencyclidine (PCP) and amphetamine have been reported in patients taking desvenlafaxine. This is due to lack of specificity of the screening tests. False positive test results may be expected for several days following discontinuation of desvenlafaxine therapy. Confirmatory tests, such as gas chromatography/mass spectrometry, will distinguish desvenlafaxine from PCP and amphetamine.

8 USE IN SPECIFIC POPULATIONS

8.1 Pregnancy

Pregnancy Exposure Registry

There is a pregnancy exposure registry that monitors pregnancy outcomes in women exposed to antidepressants during pregnancy. Healthcare providers are encouraged to register patients by calling the National Pregnancy Registry for Antidepressants at 1-844-405-6185.

Risk Summary

Based on data from published observational studies, exposure to SNRIs, particularly in the month before delivery, has been associated with a less than 2-fold increase in the risk of postpartum hemorrhage [see Warnings and Precautions (5.4) and Clinical Considerations].

There are no published studies on PRISTIQ in pregnant women; however published epidemiologic studies of pregnant women exposed to venlafaxine, the parent compound, have not reported a clear association with adverse developmental outcomes (see Data). There are risks associated with untreated depression in pregnancy and with exposure to SNRIs and SSRIs, including PRISTIQ, during pregnancy (see Clinical Considerations).

In reproductive developmental studies in rats and rabbits treated with desvenlafaxine succinate, there was no evidence of teratogenicity at a plasma exposure (AUC) that is up to 19-times (rats) and 0.5-times (rabbits) the exposure at an adult human dose of 100 mg per day. However, fetotoxicity and pup deaths were observed in rats at 4.5-times the AUC exposure observed with an adult human dose of 100 mg per day.

The estimated background risk of major birth defects and miscarriage for the indicated population is unknown. All pregnancies have a background risk of birth defect, loss, or other adverse outcomes. In the U.S. general population, the estimated background risk of major birth defects and miscarriage in clinically recognized pregnancies is 2–4% and 15–20%, respectively.

Clinical Considerations

Disease-Associated Maternal and/or Embryo/Fetal Risk

A prospective longitudinal study of 201 women with a history of major depression who were euthymic at the beginning of pregnancy, showed that women who discontinued antidepressant medication during pregnancy were more likely to experience a relapse of major depression than women who continued antidepressant medication.

Maternal Adverse Reactions

Exposure to PRISTIQ in mid to late pregnancy may increase the risk for preeclampsia, and exposure to PRISTIQ in the month before delivery may be associated with an increased risk of postpartum hemorrhage [see Warnings and Precautions (5.4)].

Fetal/Neonatal Adverse Reactions

Exposure to SNRIs or SSRIs in late pregnancy may lead to an increased risk for neonatal complications requiring prolonged hospitalization, respiratory support, and tube feeding. Monitor neonates who were exposed to PRISTIQ in the third trimester of pregnancy for drug discontinuation syndrome (see Data).

Data

Human Data

Published epidemiological studies of pregnant women exposed to the parent compound venlafaxine have not reported a clear association with major birth defects or miscarriage. Methodological limitations of these observational studies include possible exposure and outcome misclassification, lack of adequate controls, adjustment for confounders, and confirmatory studies; therefore, these studies cannot establish or exclude any drug-associated risk during pregnancy.

Retrospective cohort studies based on claims data have shown an association between venlafaxine use and preeclampsia, compared to depressed women who did not take an antidepressant during pregnancy. One study that assessed venlafaxine exposure in the second trimester or first half of the third trimester and preeclampsia showed an increased risk compared to unexposed depressed women [adjusted (adj) RR 1.57, 95% CI 1.29–1.91]. Preeclampsia was observed at venlafaxine doses equal to or greater than 75 mg/day and a duration of treatment >30 days. Another study that assessed venlafaxine exposure in gestational weeks 10–20 and preeclampsia showed an increased risk at doses equal to or greater than 150 mg/day. Available data are limited by possible outcome misclassification and possible confounding due to depression severity and other confounders.

Retrospective cohort studies based on claims data have suggested an association between venlafaxine use near the time of delivery or through delivery and postpartum hemorrhage. One study showed an increased risk for postpartum hemorrhage when venlafaxine exposure occurred through delivery, compared to unexposed depressed women [adj RR 2.24 (95% CI 1.69–2.97)]. There was no increased risk in women who were exposed to venlafaxine earlier in pregnancy. Limitations of this study include possible confounding due to depression severity and other confounders. Another study showed an increased risk for postpartum hemorrhage when SNRI exposure occurred for at least 15 days in the last month of pregnancy or through delivery, compared to unexposed women (adj RR 1.64–1.76). The results of this study may be confounded by the effects of depression.

Neonates exposed to SNRIs or SSRIs, late in the third trimester have developed complications requiring prolonged hospitalization, respiratory support, and tube feeding. Such complications can arise immediately upon delivery. Reported clinical findings have included respiratory distress, cyanosis, apnea, seizures, temperature instability, feeding difficulty, vomiting, hypoglycemia, hypotonia, hypertonia, hyperreflexia, tremor, jitteriness, irritability, and constant crying. These features are consistent with either a direct toxic effect of SSRIs and SNRIs or, possibly, a drug discontinuation syndrome. It should be noted that, in some cases, the clinical picture is consistent with serotonin syndrome [see Warnings and Precautions (5.2)].

Animal Data

When desvenlafaxine succinate was administered orally to pregnant rats and rabbits during the period of organogenesis at doses up to 300 mg/kg/day and 75 mg/kg/day, respectively, no teratogenic effects were observed. These doses were associated with a plasma exposure (AUC) 19 times (rats) and 0.5 times (rabbits) the AUC exposure at an adult human dose of 100 mg per day. However, fetal weights were decreased and skeletal ossification was delayed in rats in association with maternal toxicity at the highest dose, with an AUC exposure at the no-effect dose that is 4.5-times the AUC exposure at an adult human dose of 100 mg per day.

When desvenlafaxine succinate was administered orally to pregnant rats throughout gestation and lactation, there was a decrease in pup weights and an increase in pup deaths during the first four days of lactation at the highest dose of 300 mg/kg/day. The cause of these deaths is not known. The AUC exposure at the no-effect dose for rat pup mortality was 4.5-times the AUC exposure at an adult human dose of 100 mg per day. Post-weaning growth and reproductive performance of the progeny were not affected by maternal treatment with desvenlafaxine succinate at exposures 19 times the AUC exposure at an adult human dose of 100 mg per day.

8.2 Lactation

Risk Summary

Available limited data from published literature show low levels of desvenlafaxine in human milk, and have not shown adverse reactions in breastfed infants (see Data). There are no data on the effects of desvenlafaxine on milk production.

The developmental and health benefits of breastfeeding should be considered along with the mother's clinical need for PRISTIQ and any potential adverse effects on the breastfed child from PRISTIQ or from the underlying maternal condition.

Data

A lactation study was conducted in 10 breastfeeding women (at a mean of 4.3 months post-partum) who were being treated with a 50–150 mg daily dose of desvenlafaxine for postpartum depression. Sampling was performed at steady state (up to 8 samples) over a 24 hour dosing period, and included foremilk and hindmilk. The mean relative infant dose was calculated to be 6.8% (range of 5.5–8.1%). No adverse reactions were seen in the infants.

8.4 Pediatric Use

The safety and effectiveness of PRISTIQ have not been established in pediatric patients for the treatment of MDD.

Efficacy was not demonstrated in two adequate and well controlled, 8-week, randomized, double-blind, placebo-controlled, parallel group studies conducted in 587 patients (7 to 17 years of age) for the treatment of MDD.

Antidepressants, such as PRISTIQ, increase the risk of suicidal thoughts and behaviors in pediatric patients [see the Boxed Warning and Warnings and Precautions (5.1)].

PRISTIQ was associated with a decrease in body weight in placebo-controlled trials in pediatric patients with MDD. The incidence of weight loss (≥3.5% of baseline weight) was 22%, 14%, and 7% for patients treated with low dose PRISTIQ, high dose PRISTIQ, and placebo, respectively.

The risks associated with longer term PRISTIQ use were assessed in 6-month, open-label extension studies in pediatric patients (7 to 17 years of age) with MDD. Pediatric patients (7 to 17 years of age) had mean changes in weight that approximated expected changes, based on data from age- and sex-matched peers.

In clinical trials, when compared to adult patients receiving the same dose of PRISTIQ, exposure to desvenlafaxine was similar in adolescent patients 12 to 17 years of age, and was about 30% higher in pediatric patients 7 to 11 years of age.

Juvenile Animal Studies

In a juvenile animal study, male and female rats were treated with desvenlafaxine (75, 225 and 675 mg/kg/day) starting on postnatal day (PND) 22 through 112. Behavioral deficits (longer time immobile in a motor activity test, longer time swimming in a straight channel test, and lack of habituation in an acoustic startle test) were observed in males and females but were reversed after a recovery period. A No Adverse Effect Level (NOAEL) was not identified for these deficits. The Low Adverse Effect Level (LOAEL) was 75 mg/kg/day which was associated with plasma exposure (AUC) twice the levels measured with a pediatric dose of 100 mg/day.

In a second juvenile animal study, male and female rats were administered desvenlafaxine (75, 225 or 675 mg/kg/day) for 8–9 weeks starting on PND 22 and were mated with naïve counterparts. Delays in sexual maturation and decreased fertility, number of implantation sites and total live embryos were observed in treated females at all doses. The LOAEL for these findings is 75 mg/kg/day which was associated with an AUC twice the levels measured with a pediatric dose of 100 mg/day. These findings were reversed at the end of a 4-week recovery period. The relevance of these findings to humans is not known.

8.5 Geriatric Use

Of the 4,158 patients in pre-marketing clinical studies with PRISTIQ, 6% were 65 years of age or older. No overall differences in safety or efficacy were observed between these patients and younger patients; however, in the short-term placebo-controlled studies, there was a higher incidence of systolic orthostatic hypotension in patients ≥65 years of age compared to patients <65 years of age treated with PRISTIQ [see Adverse Reactions (6.1)]. For elderly patients, possible reduced renal clearance of PRISTIQ should be considered when determining dose [see Dosage and Administration (2.2) and Clinical Pharmacology (12.3)].

SSRIs and SNRIs, including PRISTIQ, have been associated with cases of clinically significant hyponatremia in elderly patients, who may be at greater risk for this adverse event [see Warnings and Precautions (5.9)].

8.6 Renal Impairment

Adjust the maximum recommended dosage in patients with moderate or severe renal impairment (CLcr 15 to 50 mL/min, C-G), or end-stage renal disease (CLcr < 15 mL/min, C-G) [see Dosage and Administration (2.2) and Clinical Pharmacology (12.3)].

8.7 Hepatic Impairment

Adjust the maximum recommended dosage in patients with moderate to severe hepatic impairment (Child-Pugh score 7 to 15) [see Dosage and Administration (2.3) and Clinical Pharmacology (12.3)].

9 DRUG ABUSE AND DEPENDENCE

9.1 Controlled Substance

PRISTIQ is not a controlled substance.

10 OVERDOSAGE

10.1 Human Experience with Overdosage

There is limited clinical trial experience with desvenlafaxine succinate overdosage in humans. However, desvenlafaxine (PRISTIQ) is the major active metabolite of venlafaxine. Overdose experience reported with venlafaxine (the parent drug of PRISTIQ) is presented below; the identical information can be found in the Overdosage section of the venlafaxine package insert.

In postmarketing experience, overdose with venlafaxine (the parent drug of PRISTIQ) has occurred predominantly in combination with alcohol and/or other drugs. The most commonly reported events in overdosage include tachycardia, changes in level of consciousness (ranging from somnolence to coma), mydriasis, seizures, and vomiting. Electrocardiogram changes (e.g., prolongation of QT interval, bundle branch block, QRS prolongation), sinus and ventricular tachycardia, bradycardia, hypotension, rhabdomyolysis, vertigo, liver necrosis, serotonin syndrome, and death have been reported.

Published retrospective studies report that venlafaxine overdosage may be associated with an increased risk of fatal outcomes compared to that observed with SSRI antidepressant products, but lower than that for tricyclic antidepressants. Epidemiological studies have shown that venlafaxine-treated patients have a higher pre-existing burden of suicide risk factors than SSRI-treated patients. The extent to which the finding of an increased risk of fatal outcomes can be attributed to the toxicity of venlafaxine in overdosage, as opposed to some characteristic(s) of venlafaxine-treated patients, is not clear.

10.2 Management of Overdosage

No specific antidotes for PRISTIQ are known. In managing over dosage, consider the possibility of multiple drug involvement. In case of overdose, call Poison Control Center at 1-800-222-1222 for latest recommendations.

11 DESCRIPTION

PRISTIQ is an extended-release tablet for oral administration that contains desvenlafaxine succinate, a structurally novel SNRI for the treatment of MDD. Desvenlafaxine (O-desmethylvenlafaxine) is the major active metabolite of the antidepressant venlafaxine, a medication used to treat major depressive disorder.

Desvenlafaxine is designated RS-4-[2-dimethylamino-1-(1-hydroxycyclohexyl)ethyl]phenol and has the empirical formula of C16H25NO2 (free base) and C16H25NO2∙C4H6O4∙H2O (succinate monohydrate). Desvenlafaxine succinate monohydrate has a molecular weight of 399.48. The structural formula is shown below.

Desvenlafaxine succinate is a white to off-white powder that is soluble in water. The solubility of desvenlafaxine succinate is pH dependent. Its octanol:aqueous system (at pH 7.0) partition coefficient is 0.21.

PRISTIQ is formulated as an extended-release tablet for once-a-day oral administration.

Each tablet contains 38 mg, 76 mg or 152 mg of desvenlafaxine succinate equivalent to 25 mg, 50 mg or 100 mg of desvenlafaxine, respectively.

Inactive ingredients for the 25 mg tablet consist of hypromellose, microcrystalline cellulose, talc, magnesium stearate, a film coating which consists of polyvinyl alcohol, polyethylene glycol, talc, titanium dioxide, and iron oxides.

Inactive ingredients for the 50 mg tablet consist of hypromellose, microcrystalline cellulose, talc, magnesium stearate and film coating, which consists of polyvinyl alcohol, polyethylene glycol, talc, titanium dioxide, and iron oxides.

Inactive ingredients for the 100 mg tablet consist of hypromellose, microcrystalline cellulose, talc, magnesium stearate and film coating, which consists of polyvinyl alcohol, polyethylene glycol, talc, titanium dioxide, iron oxide and FD&C yellow #6.

12 CLINICAL PHARMACOLOGY

12.1 Mechanism of Action

The exact mechanism of the antidepressant action of desvenlafaxine is unknown, but is thought to be related to the potentiation of serotonin and norepinephrine in the central nervous system, through inhibition of their reuptake. Non-clinical studies have shown that desvenlafaxine is a potent and selective SNRI.

12.2 Pharmacodynamics

Desvenlafaxine lacked significant affinity for numerous receptors, including muscarinic-cholinergic, H1-histaminergic, or α1-adrenergic receptors in vitro. Desvenlafaxine also lacked monoamine oxidase (MAO) inhibitory activity.

ECG changes

Electrocardiograms were obtained from 1,492 desvenlafaxine treated patients with major depressive disorder and 984 placebo-treated patients in clinical studies lasting up to 8 weeks. No clinically relevant differences were observed between desvenlafaxine treated and placebo-treated patients for QT, QTc, PR, and QRS intervals. In a thorough QTc study with prospectively determined criteria, desvenlafaxine did not cause QT prolongation. No difference was observed between placebo and desvenlafaxine treatments for the QRS interval.

12.3 Pharmacokinetics

The single-dose pharmacokinetics of desvenlafaxine are linear and dose-proportional in a dose range of 50 to 600 mg (1 to 12 times the recommended approved dosage) per day. With once-daily dosing, steady-state plasma concentrations are achieved within approximately 4 to 5 days. At steady-state, multiple-dose accumulation of desvenlafaxine is linear and predictable from the single-dose pharmacokinetic profile.

Absorption

The absolute oral bioavailability of PRISTIQ after oral administration is about 80%.

Effect of Food

Ingestion of a high-fat meal (800 to 1000 calories) increased desvenlafaxine Cmax about 16% and had no effect on AUC.

Distribution

Steady-state volume of distribution of desvenlafaxine is 3.4 L/kg. Plasma protein binding of desvenlafaxine is 30% and is independent of drug concentration.

Elimination

Metabolism

Desvenlafaxine is primarily metabolized by conjugation (mediated by UGT isoforms) and, to a minor extent, through oxidative metabolism. CYP3A4 mediates the oxidative metabolism (N-demethylation) of desvenlafaxine. The CYP2D6 metabolic pathway is not involved. The pharmacokinetics of desvenlafaxine was similar in subjects with CYP2D6 poor and extensive metabolizer phenotype.

Excretion

Approximately 45% of desvenlafaxine is excreted unchanged in urine at 72 hours after oral administration. Approximately 19% of the administered dose is excreted as the glucuronide metabolite and <5% as the oxidative metabolite (N,O-didesmethylvenlafaxine) in urine.

Specific Populations

No clinically significant differences in the exposures of desvenlafaxine were observed based on ethnicity (White, Black, Hispanic).

The effect of intrinsic patient factors on the pharmacokinetics of desvenlafaxine is presented in Figure 1.

Figure 1 Impact of Intrinsic Factors (Renal, Hepatic Impairment and Population Description) on Desvenlafaxine Pharmacokinetics

Drug Interaction Studies

Clinical Studies

Other Drugs on PRISTIQ

The effect of ketoconazole on the exposures of desvenlafaxine is summarized in Figure 2.

Figure 2. Effect of Other Drugs on Desvenlafaxine Pharmacokinetics

PRISTIQ on Other Drugs

The effects of PRISTIQ on the exposures of other drugs are summarized in Figure 3.

Figure 3. Effects of PRISTIQ on Pharmacokinetics of Other Drugs

In Vitro Studies

Based on in vitro data, drugs that inhibit CYP isozymes 1A1, 1A2, 2A6, 2D6, 2C8, 2C9, 2C19, and 2E1 are not expected to have significant impact on the pharmacokinetic profile of desvenlafaxine.

Desvenlafaxine does not inhibit CYP1A2, 2A6, 2C8, 2C9, 2C19 CYP2D6, or CYP3A4 isozymes. Desvenlafaxine does not induce CYP3A4 either.

Desvenlafaxine is not a substrate or an inhibitor for the P-glycoprotein (P-gp) transporter.

13 NONCLINICAL TOXICOLOGY

13.1 Carcinogenesis, Mutagenesis, Impairment of Fertility

Carcinogenesis

Desvenlafaxine succinate administered by oral gavage to mice and rats for 2 years did not increase the incidence of tumors in either study.

Mice received desvenlafaxine succinate at dosages up to 500/300 mg/kg/day (dosage lowered after 45 weeks of dosing). The AUC exposure at 300 mg/kg/day dose is estimated at 10 times the AUC exposure at an adult human dose of 100 mg per day.

Rats received desvenlafaxine succinate at dosages up to 300 mg/kg/day (males) or 500 mg/kg/day (females). The AUC exposure at the highest dose is estimated at 11 (males) or 26 (females) times the AUC exposure at an adult human dose of 100 mg per day.

Mutagenesis

Desvenlafaxine was not mutagenic in the in vitro bacterial mutation assay (Ames test) and was not clastogenic in an in vitro chromosome aberration assay in cultured CHO cells, an in vivo mouse micronucleus assay, or an in vivo chromosome aberration assay in rats. Additionally, desvenlafaxine was not genotoxic in the in vitro CHO mammalian cell forward mutation assay and was negative in the in vitro BALB/c-3T3 mouse embryo cell transformation assay.

Impairment of Fertility

When desvenlafaxine succinate was administered orally to male and female rats, fertility was reduced at the high dose of 300 mg/kg/day, which is 10 (males) and 19 (females) times the AUC exposure at an adult human dose of 100 mg per day. There was no effect on fertility at 100 mg/kg/day, which is 3 (males) or 5 (females) times the AUC exposure at an adult human dose of 100 mg per day. These studies did not address reversibility of the effect on fertility. The relevance of these findings to humans is not known.

14 CLINICAL STUDIES

Major Depressive Disorder

The efficacy of PRISTIQ as a treatment for depression was established in four 8-week, randomized, double-blind, placebo-controlled, fixed-dose studies (at doses of 50 mg per day to 400 mg per day) in adult outpatients who met the Diagnostic and Statistical Manual of Mental Disorders (DSM-IV) criteria for major depressive disorder. In the first study, patients received 100 mg (n = 114), 200 mg (n = 116), or 400 mg (n = 113) of PRISTIQ once daily, or placebo (n = 118). In a second study, patients received either 200 mg (n = 121) or 400 mg (n = 124) of PRISTIQ once daily, or placebo (n = 124). In two additional studies, patients received 50 mg (n = 150 and n = 164) or 100 mg (n = 147 and n = 158) of PRISTIQ once daily, or placebo (n = 150 and n = 161).

PRISTIQ showed superiority over placebo as measured by improvement in the 17-item Hamilton Rating Scale for Depression (HAM-D17) total score in four studies and overall improvement, as measured by the Clinical Global Impressions Scale - Improvement (CGI-I), in three of the four studies. In studies directly comparing 50 mg per day and 100 mg per day there was no suggestion of a greater effect with the higher dose and adverse reactions and discontinuations were more frequent at higher doses [see Dosage and Administration (2.1)].

Table 9: Primary Efficacy (HAM-D17) Results for Short-term Studies
 |  |  | PRISTIQ
Study No. | Primary Endpoint: HAM-D17 | Placebo | 50 mg/day | 100 mg/day | 200 mg/day | 400 mg/day
1 | Baseline Score (SD [Standard deviation.]) | 23.1 (2.5) |  | 23.2 (2.5) | 22.9 (2.4) | 23.0 (2.2)
 | Difference from Placebo (95% CI [Difference between least squares means at final evaluation, calculated as drug response minus placebo response; unadjusted 95% confidence intervals.]) |  |  | -2.9 [Adjusted p-value < 0.05.] (-5.1, -0.8) | -2.0 | -3.1 (-5.2, -0.9)
2 | Baseline Score (SD) | 25.3 (3.3) |  |  | 24.8 (2.9) | 25.2 (3.2)
 | Difference from Placebo (95% CI) |  |  |  | -3.3 (-5.3, -1.2) | -2.8 (-4.8, -0.7)
3 | Baseline Score (SD) | 23.0 (2.6) | 23.4 (2.6) | 23.4 (2.6)
 | Difference from Placebo (95% CI) |  | -1.9 (-3.5, -0.3) | -1.5
4 | Baseline Score (SD) | 24.3 (2.6) | 24.3 (2.4) | 24.4 (2.7)
 | Difference from Placebo (95% CI) |  | -2.5 (-4.1, -0.9) | -3.0 (-4.7, -1.4)

Analyses of the relationships between treatment outcome and age and treatment outcome and gender did not suggest any differential responsiveness on the basis of these patient characteristics. There was insufficient information to determine the effect of race on outcome in these studies.

In a longer-term trial (Study 5), adult outpatients meeting DSM-IV criteria for major depressive disorder, who responded to 8 weeks of open-label acute treatment with 50 mg per day desvenlafaxine and subsequently remained stable for 12 weeks on desvenlafaxine, were assigned randomly in a double-blind manner to remain on active treatment or switch to placebo for up to 26 weeks of observation for relapse. Response during the open-label phase was defined as a HAM-D17 total score of ≤ 11 and CGI-I ≤ 2 at the day 56 evaluation; stability was defined as HAM-D17 total score of ≤ 11 and CGI-I ≤ 2 at week 20 and not having a HAM-D17 total score of ≥ 16 or a CGI-I score ≥ 4 at any office visit. Relapse during the double-blind phase was defined as follows: (1) a HAM-D17 total score of ≥ 16 at any office visit, (2) discontinuation for unsatisfactory efficacy response, (3) hospitalized for depression, (4) suicide attempt, or (5) suicide. Patients receiving continued desvenlafaxine treatment experienced statistically significantly longer time to relapse compared with placebo. At 26 weeks, the Kaplan-Meier estimated proportion of relapse was 14% with desvenlafaxine treatment versus 30% with placebo.

Figure 4. Estimated Proportion of Relapses vs. Number of Days since Randomization (Study 5)

In another longer-term trial (Study 6), adult outpatients meeting DSM-IV criteria for major depressive disorder and who responded to 12 weeks of acute treatment with desvenlafaxine were assigned randomly to the same dose (200 or 400 mg per day) they had received during acute treatment or to placebo for up to 26 weeks of observation for relapse. Response during the open-label phase was defined as a HAM-D17 total score of ≤ 11 at the day 84 evaluation. Relapse during the double-blind phase was defined as follows: (1) a HAM-D17 total score of ≥ 16 at any office visit, (2) a CGI-I score of ≥ 6 (versus day 84) at any office visit, or (3) discontinuation from the trial due to unsatisfactory response. Patients receiving continued desvenlafaxine treatment experienced statistically significantly longer time to relapse over the subsequent 26 weeks compared with those receiving placebo. At 26 weeks, the Kaplan-Meier estimated proportion of relapse was 29% with desvenlafaxine treatment versus 49% with placebo.

Figure 5. Estimated Proportion of Relapses vs. Number of Days since Randomization (Study 6)

In a postmarketing study, the efficacy of PRISTIQ at a dose lower than 50 mg per day was evaluated in an 8-week, multicenter, randomized, double-blind, placebo-controlled, fixed-dose study in adult outpatients with Major Depressive Disorder. The treatment arms were 25 mg (n=232), 50 mg (n=236), and placebo (n=231). The 50 mg dose was superior to placebo, as measured by the mean change from baseline on the HAMD-17. The 25 mg dose was not superior to placebo.

16 HOW SUPPLIED/STORAGE AND HANDLING

PRISTIQ® (desvenlafaxine) extended-release tablets are available as follows:

25 mg, tan, square pyramid tablet debossed with "W" (over) "25" on the flat side

NDC 0008-1210-30, bottle of 30 tablets in unit-of-use package

50 mg, light pink, square pyramid tablet debossed with "W" (over) "50" on the flat side

NDC 0008-1211-14, bottle of 14 tablets in unit-of-use package
NDC 0008-1211-30, bottle of 30 tablets in unit-of-use package
NDC 0008-1211-01, bottle of 90 tablets in unit-of-use package
NDC 0008-1211-50, 10 blisters of 10 (HUD)

100 mg, reddish-orange, square pyramid tablet debossed with "W" (over) "100" on the flat side

NDC 0008-1222-14, bottle of 14 tablets in unit-of-use package
NDC 0008-1222-30, bottle of 30 tablets in unit-of-use package
NDC 0008-1222-01, bottle of 90 tablets in unit-of-use package
NDC 0008-1222-50, 10 blisters of 10 (HUD)

STORAGE AND HANDLING

Store at 20° to 25°C (68° to 77°F); excursions permitted to 15° to 30°C (59° to 86°F) [see USP Controlled Room Temperature].

Each tablet contains 38 mg, 76 mg or 152 mg of desvenlafaxine succinate equivalent to 25 mg, 50 mg or 100 mg of desvenlafaxine, respectively.

17 PATIENT COUNSELING INFORMATION

Advise the patient to read the FDA-approved patient labeling (Medication Guide).

Suicidal Thoughts and Behaviors

Advise patients and caregivers to look for the emergence of suicidality, especially early during treatment and when the dose is adjusted up or down, and instruct them to report such symptoms to the healthcare provider [see Boxed Warning and Warnings and Precautions (5.1)].

Concomitant Medication

Advise patients taking PRISTIQ not to use concomitantly other products containing desvenlafaxine or venlafaxine. Healthcare professionals should instruct patients not to take PRISTIQ with an MAOI or within 14 days of stopping an MAOI and to allow 7 days after stopping PRISTIQ before starting an MAOI [see Contraindications (4)].

Serotonin Syndrome

Caution patients about the risk of serotonin syndrome, particularly with the concomitant use of PRISTIQ with other serotonergic agents (including triptans, tricyclic antidepressants, opioids, lithium, amphetamines, tryptophan, buspirone, and St. John's Wort supplements) [see Warnings and Precautions (5.2)].

Elevated Blood Pressure

Advise patients that they should have regular monitoring of blood pressure when taking PRISTIQ [see Warnings and Precautions (5.3)].

Increased Risk of Bleeding

Inform patients about the concomitant use of PRISTIQ with NSAIDs, aspirin, other antiplatelet drugs, warfarin, or other coagulants because the combined use of has been associated with an increased risk of bleeding. Advise patients to inform their healthcare providers if they are taking or planning to take any prescription or over-the-counter medications that increase the risk of bleeding [see Warnings and Precautions (5.4)].

Activation of Mania/Hypomania

Advise patients, their families and caregivers to observe for signs of activation of mania/hypomania [see Warnings and Precautions (5.6)].

Discontinuation Syndrome

Advise patients not to abruptly stop taking PRISTIQ without talking first with their healthcare professional. Patients should be aware that discontinuation effects may occur when stopping PRISTIQ, and a dose of 25 mg per day is available for discontinuing therapy [see Warnings and Precautions (5.7) and Adverse Reactions (6.1)].

Sexual Dysfunction

Advise patients that use of PRISTIQ may cause symptoms of sexual dysfunction in both male and female patients. Inform patients that they should discuss any changes in sexual function and potential management strategies with their healthcare provider [see Warnings and Precautions (5.11)].

Switching Patients from Other Antidepressants to PRISTIQ

Discontinuation symptoms have been reported when switching patients from other antidepressants, including venlafaxine, to PRISTIQ. Tapering of the initial antidepressant may be necessary to minimize discontinuation symptoms.

Interference with Cognitive and Motor Performance

Caution patients about operating hazardous machinery, including automobiles, until they are reasonably certain that PRISTIQ therapy does not adversely affect their ability to engage in such activities.

Alcohol

Advise patients to avoid alcohol while taking PRISTIQ [see Drug Interactions (7.3)].

Allergic Reactions

Advise patients to notify their physician if they develop allergic phenomena such as rash, hives, swelling, or difficulty breathing.

Pregnancy

Advise patients to notify their physician if they become pregnant or intend to become pregnant during therapy. Advise patients that there is a pregnancy exposure registry that monitors pregnancy outcomes in women exposed to PRISTIQ during pregnancy [see Use in Specific Populations (8.1)].

Residual Inert Matrix Tablet

Patients receiving PRISTIQ may notice an inert matrix tablet passing in the stool or via colostomy. Patients should be informed that the active medication has already been absorbed by the time the patient sees the inert matrix tablet.

This product's label may have been updated. For current full prescribing information, please visit www.pfizer.com.

LAB-0452-24.0

MEDICATION GUIDE
PRISTIQ® (pris-TEEK)
(desvenlafaxine)
extended-release tablets

What is the most important information I should know about PRISTIQ?
PRISTIQ can cause serious side effects, including:

- Increased risk of suicidal thoughts or actions in some children and young adults within the first few months of treatment. PRISTIQ is not for use in children.
- Depression or other serious mental illnesses are the most important causes of suicidal thoughts or actions.
  How can I watch for and try to prevent suicidal thoughts and actions?
  - Pay close attention to any changes, especially sudden changes, in mood, behaviors, thoughts, or feelings. This is very important when an antidepressant medicine is started or when the dose is changed.
  - Call the healthcare provider right away to report new or sudden changes in mood, behavior, thoughts, or feelings.
  - Keep all follow-up visits with the healthcare provider as scheduled. Call the healthcare provider between visits as needed, especially if you have concerns about symptoms.
    Call your healthcare provider right away if you have any of the following symptoms, especially if they are new, worse, or worry you:

- thoughts about suicide or dying
- attempts to commit suicide
- new or worse depression
- new or worse anxiety
- feeling very agitated or restless
- panic attacks

- trouble sleeping (insomnia)
- new or worse irritability
- acting aggressive, being angry, or violent
- acting on dangerous impulses
- an extreme increase in activity and talking (mania)
- other unusual changes in behavior or mood

What is PRISTIQ?

- PRISTIQ is a prescription medicine used to treat adults with a certain type of depression called major depressive disorder (MDD). PRISTIQ belongs to a class of medicines known as serotonin and norepinephrine reuptake inhibitors (SNRIs).

Do not take PRISTIQ if you:

- are allergic to desvenlafaxine succinate, venlafaxine hydrochloride, or any of the ingredients in PRISTIQ. See the end of this Medication Guide for a complete list of ingredients in PRISTIQ.
- take a monoamine oxidase inhibitor (MAOI).
- have stopped taking an MAOI in the last 14 days. Ask your healthcare provider or pharmacist if you are not sure if you take an MAOI.
- are being treated with the antibiotic linezolid or the intravenous methylene blue.

Do not start taking an MAOI for at least 7 days after you stop treatment with PRISTIQ.

Before taking PRISTIQ tell your healthcare provider about all your medical conditions, including if you:

- have high blood pressure
- have heart problems
- have cerebrovascular problems or had a stroke
- have or had bleeding problems
- have, or have a family history of, bipolar disorder, mania or hypomania
- have high cholesterol or high triglycerides
- have or had depression, suicidal thoughts or behavior
- have kidney or liver problems
- have or had seizures or convulsions
- have low sodium levels in your blood
- are pregnant or plan to become pregnant. Talk to your healthcare provider about the risk to your unborn baby if you take PRISTIQ during pregnancy.

- Tell your healthcare provider if you become pregnant or think you are pregnant during treatment with PRISTIQ.
- If you become pregnant during treatment with PRISTIQ, talk to your healthcare provider about registering with the National Pregnancy Registry for Antidepressants. You can register by calling 1-844-405-6185.

- are breastfeeding or plan to breastfeed. PRISTIQ can pass into your breast milk. Talk to your healthcare provider about the best way to feed your baby during treatment with PRISTIQ.

Tell your healthcare provider about all the medicines you take, including prescription and over-the-counter medicines, vitamins, and herbal supplements.
PRISTIQ and other medicines may affect each other causing possible serious side effects. PRISTIQ may affect the way other medicines work and other medicines may affect the way PRISTIQ works.
Especially tell your healthcare provider if you take:

- other MAOIs
- medicines to treat migraine headaches known as triptans
- tricyclic antidepressants
- lithium
- tramadol, fentanyl, meperidine, methadone, or other opioids
- tryptophan
- buspirone
- amphetamines
- St. John's Wort
- other medicines containing desvenlafaxine or venlafaxine
- medicines that can affect blood clotting such as aspirin, nonsteroidal anti-inflammatory drugs (NSAIDs), warfarin
- medicines used to treat mood, anxiety, psychotic, or thought disorders, including selective serotonin reuptake inhibitors (SSRIs) and serotonin norepinephrine reuptake inhibitors (SNRIs)

Ask your healthcare provider if you are not sure if you are taking any of these medicines. Your healthcare provider can tell you if it is safe to take PRISTIQ with your other medicines.
Do not start or stop any other medicines during treatment with PRISTIQ without talking to your healthcare provider first. Stopping PRISTIQ suddenly may cause you to have serious side effects. See, "What are the possible side effects of PRISTIQ?"
Know the medicines you take. Keep a list of them to show to your healthcare providers when you get a new medicine.

How should I take PRISTIQ?

- Take PRISTIQ exactly as your healthcare provider tells you to.
- Take PRISTIQ 1 time a day at about the same time each day.
- PRISTIQ may be taken either with or without food.
- Swallow PRISTIQ tablets whole, with fluid. Do not divide, crush, chew, or dissolve PRISTIQ tablets.
- When you take PRISTIQ, you may see something in your stool that looks like a tablet. This is the empty shell from the tablet after the medicine has been absorbed by your body.
- If over-exposure occurs, call your Poison Control Center at 1-800-222-1222 or go to the nearest hospital emergency room right away.

What should I avoid while taking PRISTIQ?

- Do not drive a car or operate heavy machinery until you know how PRISTIQ affects you.
- You should not drink alcohol while taking PRISTIQ.

What are the possible side effects of PRISTIQ?
PRISTIQ can cause serious side effects, including:

- See, "What is the most important information I should know about PRISTIQ?"
- Serotonin syndrome. A potentially life-threatening problem called serotonin syndrome can happen when you take PRISTIQ with certain other medicines. See, "Do not take PRISTIQ if you:" Call your healthcare provider or go to the nearest hospital emergency room right away if you have any of the following signs and symptoms of serotonin syndrome:

- agitation
- confusion
- fast heart beat
- dizziness
- flushing
- tremors, stiff muscles, or muscle twitching
- seizures

- seeing or hearing things that are not real (hallucinations)
- coma
- changes in blood pressure
- sweating
- high body temperature (hyperthermia)
- loss of coordination
- nausea, vomiting, diarrhea

- New or worsened high blood pressure (hypertension). Your healthcare provider should check your blood pressure before and during treatment with PRISTIQ. If you have high blood pressure, it should be controlled before you start treatment with PRISTIQ.
- Increased chance of bleeding or bruising. Taking PRISTIQ with aspirin, NSAIDs, or blood thinners may add to this risk. Tell your healthcare provider right away about any unusual bleeding or bruising.
- Eye problems (angle closure glaucoma). Many antidepressant medicines, including PRISTIQ, may cause a certain type of eye problem called angle-closure glaucoma. Call your healthcare provider if you have changes in your vision or eye pain.
- Discontinuation syndrome. Suddenly stopping PRISTIQ when you take higher doses may cause you to have serious side effects. Your healthcare provider may want to decrease your dose slowly. Symptoms may include the following, some of which can be severe and last for a long time:

- dizziness
- irritability and agitation
- anxiety
- sweating
- aggressiveness (including hostility, rage)
- tremor
- sweating
- seizures

- ringing in your ears (tinnitus)
- nausea
- problems sleeping
- tiredness
- confusion
- electric shock sensation (paresthesia)

- headache
- diarrhea
- abnormal dreams
- changes in your mood
- hypomania
- problems with eyesight (such as blurred vision and trouble focusing)
- increase in blood pressure

- Seizures (convulsions).
- Low sodium levels in your blood (hyponatremia). Low sodium levels can happen during treatment with PRISTIQ. Low sodium levels in your blood may be serious and may cause death. Signs and Symptoms of low sodium levels in your blood may include:
  - headache
  - difficulty concentrating
  - memory changes
  - confusion
  - weakness and unsteadiness on your feet which can lead to falls
In severe or more sudden cases, signs and symptoms include:
  1. hallucinations (seeing or hearing things that are not real)
  2. fainting
  3. seizures
  4. coma
- Lung problems. Some people who have taken the medicine venlafaxine which is the same kind of medicine as the medicine in PRISTIQ have had lung problems. Symptoms of lung problems include difficulty breathing, cough, or chest discomfort. Tell your healthcare provider right away if you have any of these symptoms.
- Sexual Problems (dysfunction). Taking serotonin and norepinephrine reuptake inhibitors (SNRIs), including PRISTIQ, may cause sexual problems.
  Symptoms in males may include:
  - Delayed ejaculation or inability to have an ejaculation
  - Decreased sex drive
  - Problems getting or keeping an erection
Symptoms in females may include:
  1. Decreased sex drive
  2. Delayed orgasm or inability to have an orgasm
Talk to your healthcare provider if you develop any changes in your sexual function or if you have any questions or concerns about sexual problems during treatment with PRISTIQ. There may be treatments your healthcare provider can suggest.

The most common side effects of PRISTIQ include:

- nausea
- problems sleeping
- constipation
- decreased appetite
- sexual function problems

- dizziness
- sweating
- feeling sleepy
- anxiety

These are not all the possible side effects of PRISTIQ.
Call your doctor for medical advice about side effects. You may report side effects to FDA at 1-800-FDA-1088.

How should I store PRISTIQ?

- Store PRISTIQ at room temperature between 68°F to 77°F (20°C to 25°C).
- Keep PRISTIQ and all medicines out of the reach of children.

General Information about the safe and effective use of PRISTIQ
Medicines are sometimes prescribed for purposes other than those listed in a Medication Guide. Do not take PRISTIQ for a condition for which it was not prescribed. Do not give PRISTIQ to other people, even if they have the same symptoms that you have. It may harm them. You can ask your pharmacist or healthcare provider for information about PRISTIQ that is written for healthcare professionals.

What are the ingredients in PRISTIQ?
Active ingredient: desvenlafaxine
Inactive ingredients:

- 25 mg tablet: hypromellose, microcrystalline cellulose, talc, magnesium stearate, a film coating which consists of polyvinyl alcohol, polyethylene glycol, talc, titanium dioxide, and iron oxides.
- 50 mg tablet: hypromellose, microcrystalline cellulose, talc, magnesium stearate and film coating, which consists of polyvinyl alcohol, polyethylene glycol, talc, titanium dioxide, and iron oxides.
- 100 mg tablet: hypromellose, microcrystalline cellulose, talc, magnesium stearate, a film coating which consists of polyvinyl alcohol, polyethylene glycol, talc, titanium dioxide, iron oxide and FD&C yellow #6.

This product's label may have been updated. For current full prescribing information, please visit www.pfizer.com.

LAB-0539-15.0

For more information, go to www.pristiq.com or call 1-888-PRISTIQ (774-7847).

This Medication Guide has been approved by the U.S. Food and Drug Administration. Revised: 6/2024

PRINCIPAL DISPLAY PANEL - 50 mg Tablet Blister Pack

NDC 0008-1211-50
Pristiq®
(desvenlafaxine)

Extended-Release
Tablets
50 mg*

*Equivalent to 76 mg
desvenlafaxine succinate
MADE IN SINGAPORE

PAA041479

Wyeth® Phila., PA 19101

PRINCIPAL DISPLAY PANEL - 50 mg Tablet Blister Pack Carton

ALWAYS DISPENSE WITH MEDICATION GUIDE

Pfizer
NDC 0008-1211-50

10 Redipak® Blister
Strips of 10 Tablets

Pristiq®
(desvenlafaxine)
Extended-Release Tablets

50 mg*

100 Tablets
Rx only

PRINCIPAL DISPLAY PANEL - 50 mg Tablet Bottle Label

ALWAYS DISPENSE WITH MEDICATION GUIDE

Pfizer
NDC 0008-1211-30

Pristiq®
(desvenlafaxine)
Extended-Release Tablets

50 mg*

Unit of Use
30 Tablets
Rx only

PRINCIPAL DISPLAY PANEL - 100 mg Tablet Bottle Label

ALWAYS DISPENSE WITH MEDICATION GUIDE

Pfizer
NDC 0008-1222-30

Pristiq®
(desvenlafaxine)
Extended-Release Tablets

100 mg*

Unit of Use
30 Tablets
Rx only

PRINCIPAL DISPLAY PANEL - 100 mg Tablet Blister Pack

NDC 0008-1222-50
Pristiq®
(desvenlafaxine)

Extended-Release
Tablets
100 mg*

*Equivalent to 152 mg
desvenlafaxine succinate
MADE IN SINGAPORE

PAA041470

Wyeth® Phila., PA 19101

PRINCIPAL DISPLAY PANEL - 100 mg Tablet Blister Pack Carton

ALWAYS DISPENSE WITH MEDICATION GUIDE

Pfizer
NDC 0008-1222-50

10 Redipak® Blister
Strips of 10 Tablets

Pristiq®
(desvenlafaxine)
Extended-Release Tablets

100 mg*

100 Tablets
Rx only

PRINCIPAL DISPLAY PANEL - 25 mg Tablet Bottle Label

ALWAYS DISPENSE WITH MEDICATION GUIDE

Pfizer
NDC 0008-1210-30

Pristiq®
(desvenlafaxine)
Extended-Release Tablets

25 mg*

Unit of Use
30 Tablets
Rx only